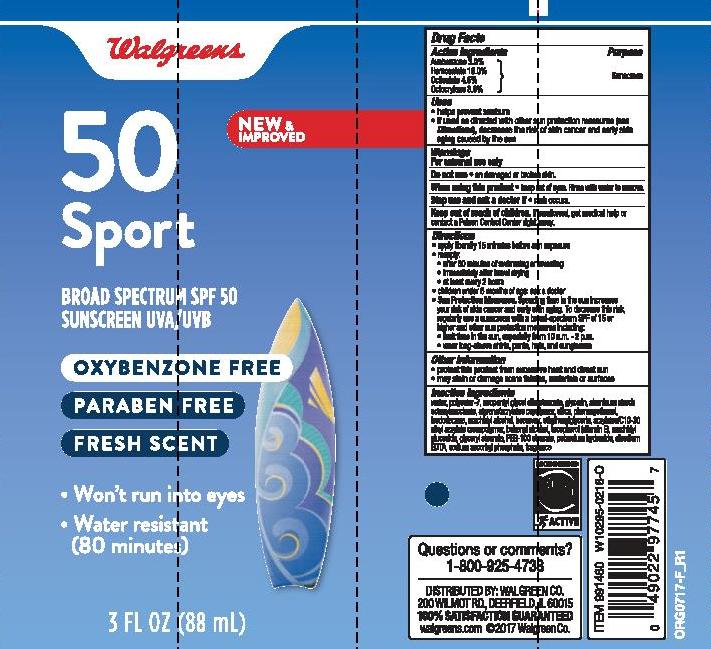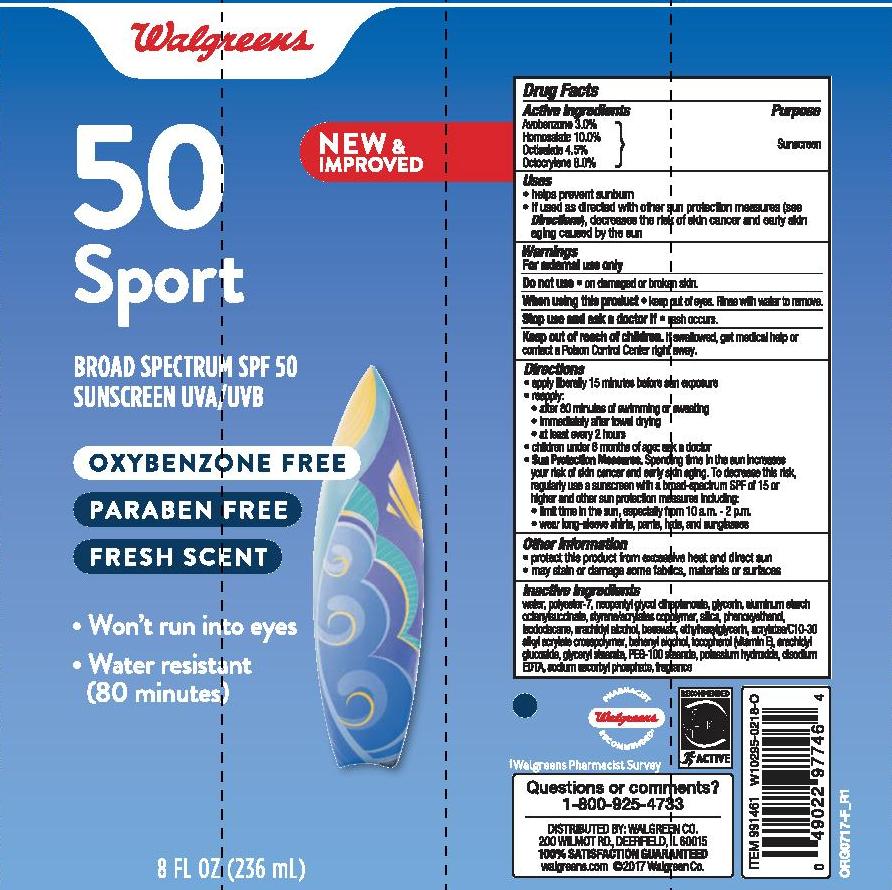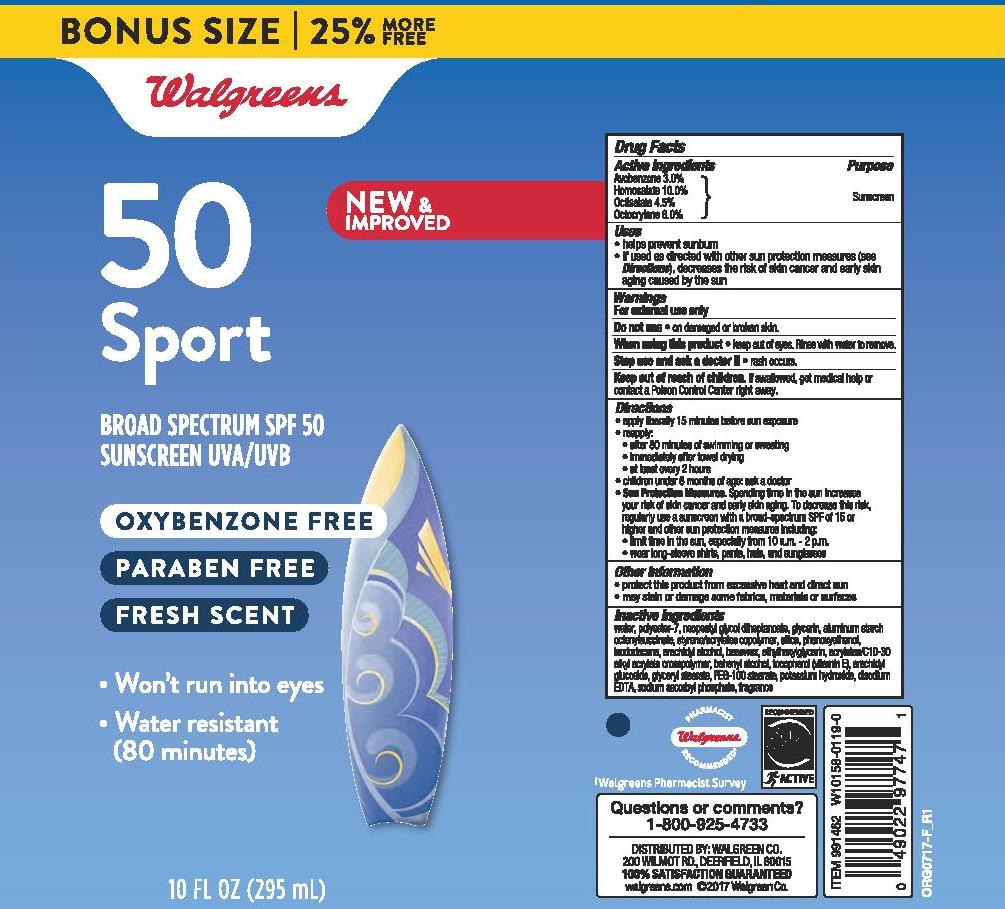 DRUG LABEL: WALGREENS BROAD SPECTRUM SPORT SPF 50 SUNSCREEN
NDC: 0363-0943 | Form: LOTION
Manufacturer: WALGREEN COMPANY
Category: otc | Type: HUMAN OTC DRUG LABEL
Date: 20241014

ACTIVE INGREDIENTS: AVOBENZONE 30 mg/1 mL; HOMOSALATE 100 mg/1 mL; OCTISALATE 45 mg/1 mL; OCTOCRYLENE 80 mg/1 mL
INACTIVE INGREDIENTS: BUTYL METHACRYLATE/METHYL METHACRYLATE/METHACRYLIC ACID/STYRENE CROSSPOLYMER; WATER; GLYCERIN; POLYESTER-7; NEOPENTYL GLYCOL DIHEPTANOATE; ALUMINUM STARCH OCTENYLSUCCINATE; SILICON DIOXIDE; PHENOXYETHANOL; ISODODECANE; ARACHIDYL ALCOHOL; ETHYLHEXYLGLYCERIN; CARBOMER INTERPOLYMER TYPE A (ALLYL SUCROSE CROSSLINKED); DOCOSANOL; .ALPHA.-TOCOPHEROL, DL-; WHITE WAX; ARACHIDYL GLUCOSIDE; POTASSIUM HYDROXIDE; GLYCERYL STEARATE/PEG-100 STEARATE; EDETATE DISODIUM; SODIUM ASCORBYL PHOSPHATE

WALGREENS SPORT BROAD SPECTRUM SPF 50 SUNSCREEN LOTION

Active ingredients

Avobenzone 3.0%, Homosalate 10.0%, Octisalate 4.5%, Octocrylene 8.0%

Purpose

Sunscreen

Uses

- helps prevent sunburn
- if used as directed with other sun protection mesaures (see Directions), decreases the risk of skin cancer and early skin aging caused by the sun

Warnings

For external use only

Do not use

• on damaged or broken skin

When using this product

• keep out of eyes. Rinse with water to remove.

Stop use and ask a doctor if

• rash occurs

Keep out of reach of children.

If product is swallowed, get medical help or contact a Poison Control Center right away.

Directions

- apply liberally 15 minutes before sun exposure

- reapply:

• after 80 minutes of swimming or sweating

• immediately after towel drying

• at least every 2 hours

- children under 6 months: Ask a doctor

- Sun Protection Measures. Spending time in the sun increases your risk of skin cancer and early skin aging. To decrease this risk, regularly use a sunscreen with a Broad Spectrum SPF value of 15 or higher and other sun protection measures including:

• limit time in the sun, espcially from 10 a.m.-2 p.m.

• wear long-sleeved shirts, pants, hats, and sunglasses

Other information

- protect the product in this container from excessive heat and direct sun
- may stain or damage some fabrics, materials or surfaces

Inactive ingredients

water, polyester-7, neopentyl glycol diheptanoate, glycerin, aluminum starch octenylsuccinate, styrene/acrylates copolymer, silica, phenoxyethanol, isododecane, arachidyl alcohol, beeswax, ethylhexylglycerin, acrylates/C10-30 alkyl acrylate crosspolymer, behenyl alcohol, tocopherol (vitamin E), arachidyl glucoside, glyceryl stearate, PEG-100 stearate, potassium hydroxide, disodium EDTA, sodium ascorbyl phosphate, fragrance

PACKAGE LABEL

WALGREENS SPORT BROAD SPECTRUM SPF 50 SUNSCREEN LOTION

3 FL OZ (88mL)

NDC 0363-0943-09

WALGREENS SPORT BROAD SPECTRUM SPF 50 SUNSCREEN LOTION

8 FL OZ (236mL)

NDC 0363-0943-69

WALGREENS SPORT BROAD SPECTRUM SPF 50 SUNSCREEN LOTION

10 FL OZ (295mL)

NDC 0363-0943-70